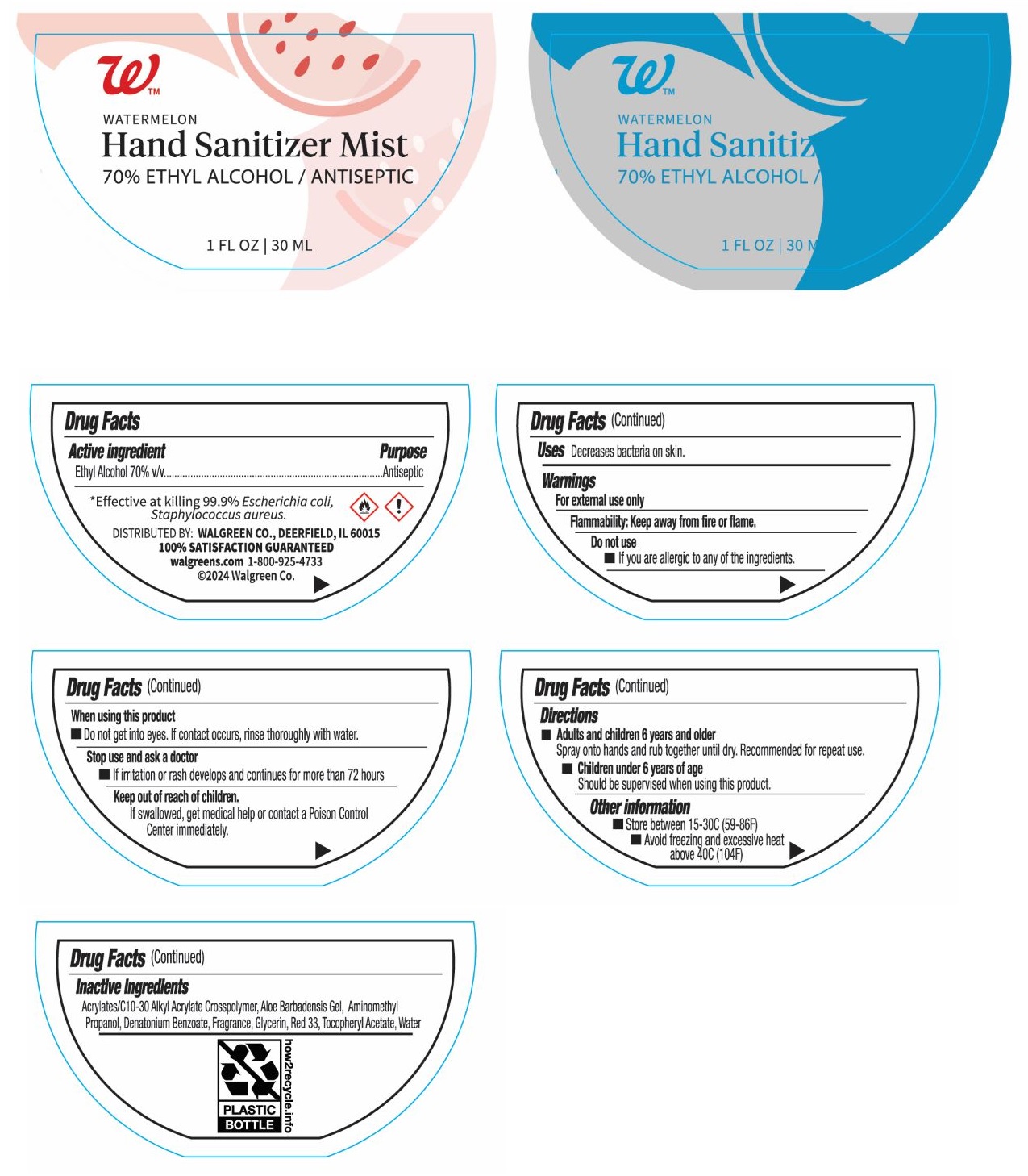 DRUG LABEL: Walgreens WATERMELON Hand Sanitizer Mist
NDC: 0363-5190 | Form: SPRAY
Manufacturer: Walgreen Company
Category: otc | Type: HUMAN OTC DRUG LABEL
Date: 20250321

ACTIVE INGREDIENTS: ALCOHOL 70 mL/100 mL
INACTIVE INGREDIENTS: ACRYLATES/C10-30 ALKYL ACRYLATE CROSSPOLYMER (60000 MPA.S); ALOE VERA LEAF; AMINOMETHYLPROPANOL; DENATONIUM BENZOATE; GLYCERIN; D&C RED NO. 33; .ALPHA.-TOCOPHEROL ACETATE; WATER

WATERMELON Hand Sanitizer Mist

Active ingredient

Ethyl Alcohol 70% v/v

Purpose

Antiseptic

Uses

Decreases bacteria on skin.

Warnings

For external use only

Flammability: Keep away from fire or flame.

Do not use
• If you are allergic to any of the ingredients.

When using this product
• Do not get into eyes. If contact occurs, rinse thoroughly with water.

Stop use and ask a doctor
• If irritation or rash develops and continues for more than 72 hours

Keep out of reach of children.
If swallowed, get medical help or contact a Poison Control Center immediately.

Directions

• Adults and children 6 years and older
Spray onto hands and rub together until dry. Recommended for repeat use.

• Children under 6 years of age
Should be supervised when using this product.

Other information

• Store between 15-30C (59-86F)
• Avoid freezing and excessive heat above 40C (104F)

Inactive ingredients

Acrylates/C10-30 Alkyl Acrylate Crosspolymer, Aloe Barbadensis Gel, Aminomethyl Propanol, Denatonium Benzoate, Fragrance, Glycerin, Red 33, Tocopheryl Acetate, Water

*Effective at killing 99.9% Escherichia coli, Staphylococcus aureus.

DISTRIBUTED BY: WALGREEN CO., DEERFIELD, IL 60015
100% SATISFACTION GUARANTEED
walgreens.com 1-800-925-4733
©2024 Walgreen Co.